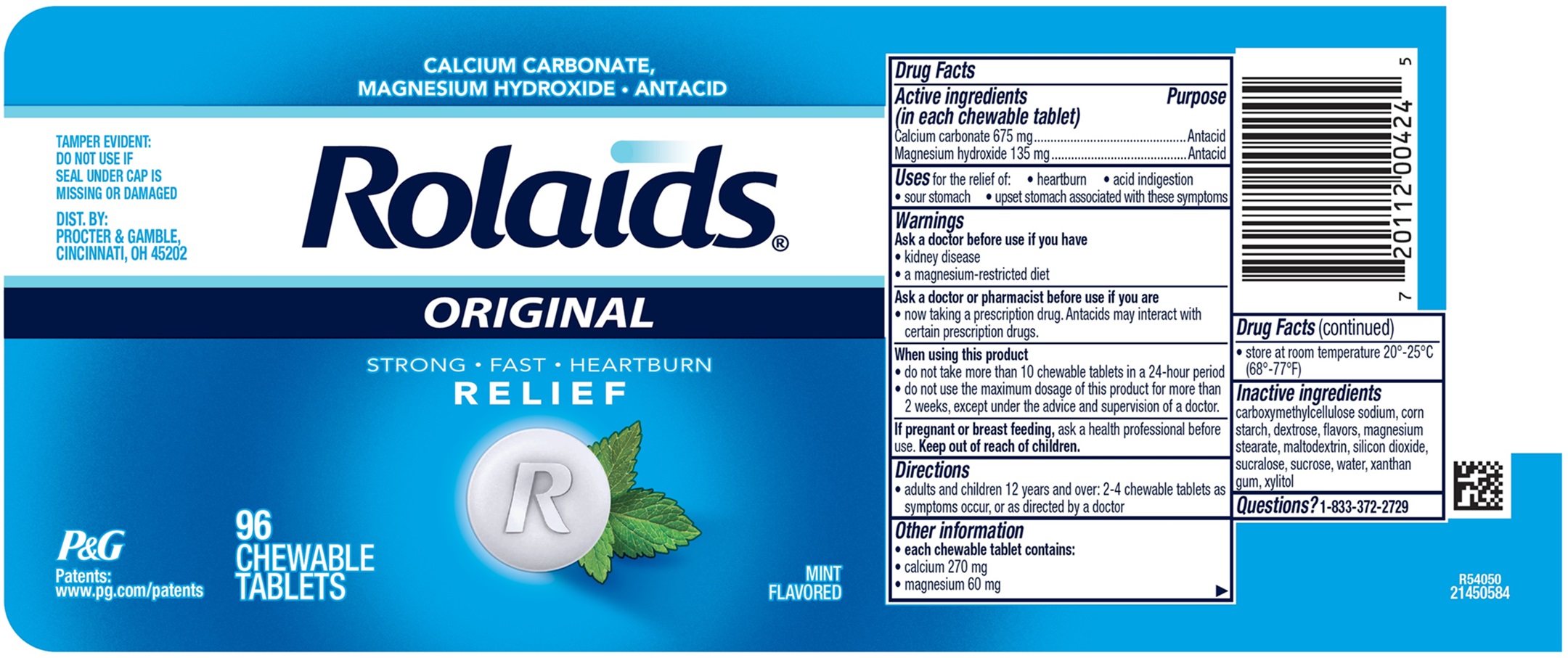 DRUG LABEL: Rolaids ORIGINAL
NDC: 84126-324 | Form: TABLET, CHEWABLE
Manufacturer: THE PROCTER & GAMBLE MANUFACTURING COMPANY
Category: otc | Type: HUMAN OTC DRUG LABEL
Date: 20251202

ACTIVE INGREDIENTS: CALCIUM CARBONATE 675 mg/1 1; MAGNESIUM HYDROXIDE 135 mg/1 1
INACTIVE INGREDIENTS: CARBOXYMETHYLCELLULOSE SODIUM; DEXTROSE; MAGNESIUM STEARATE; SILICON DIOXIDE; SUCRALOSE; SUCROSE; WATER; XANTHAN GUM; XYLITOL; STARCH, CORN; MALTODEXTRIN

Rolaids ORIGINAL

Rolaids ORIGINAL

Drug Facts

Active ingredient (in each chewable tablet)

Calcium carbonate 675 mg
Magnesium hydroxide 135 mg

Purpose

Antacid

Antacid

Uses

for the relief of:

- heartburn
- acid indigestion
- sour stomach
- upset stomach associated with these symptoms

Warnings

Ask a doctor before use if you have

- kidney disease
- a magnesium-restricted diet

Ask a doctor or pharmacist before use if you

- are now taking a prescription drug. Antacids may interact with certain prescription drugs.

When using this product

- do not take more than 10 tablets in a 24-hour period
- do not use the maximum dosage for more than 2 weeks, except under the advice and supervision of a doctor.

Directions

- adults and children 12 years and over; 2-4 chewable tablets as symptoms occur, or as directed by a doctor

Other information

- each chewable tablet contains:
- calcium 270 mg
- magnesium 60 mg
- store at room temperature 20º -25ºC (68º -77ºF)

Inactive ingredients

carboxymethylcellulose sodium, corn starch, dextrose, flavors, magnesium stearate, maltodextrin, silicon dioxide, sucralose, sucrose, water, xanthan gum, xylitol

TAMPER EVIDENT: DO NOT USE IF SEAL UNDER CAP IS MISSING OR DAMAGED

DIST. BY: PROCTER &

GAMBLE, CINCINNATI, OH

45202

PRINCIPAL DISPLAY PANEL

CALCIUM CARBONATE, MAGNESIUM HYDROXIDE • ANTACID

Rolaids

ORIGINAL

STRONG • FAST • HEARTBURN

RELIEF

MINT FLAVORED

96 CHEWABLE TABLETS